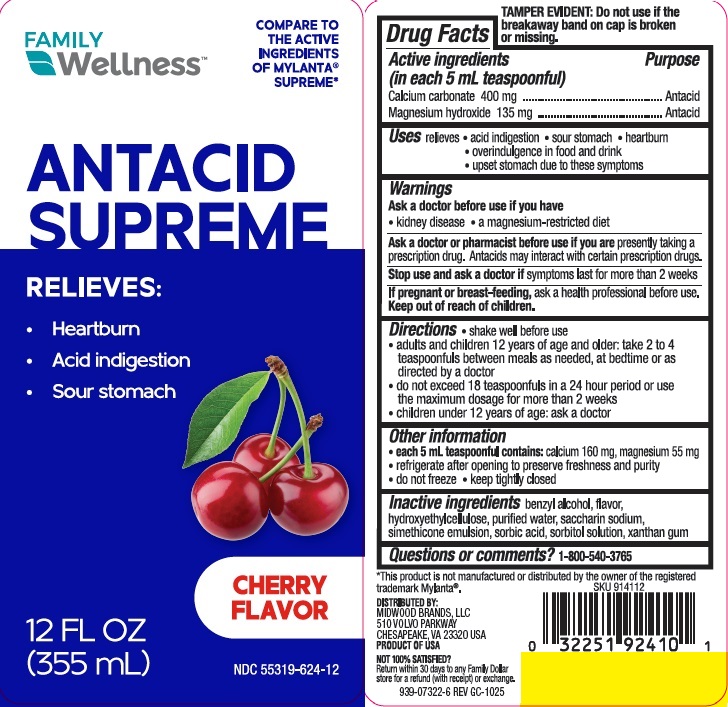 DRUG LABEL: SUPREME ANTACID
NDC: 55319-624 | Form: SUSPENSION
Manufacturer: FAMILY DOLLAR SERVICES INC
Category: otc | Type: HUMAN OTC DRUG LABEL
Date: 20251119

ACTIVE INGREDIENTS: CALCIUM CARBONATE 400 mg/5 mL; MAGNESIUM HYDROXIDE 135 mg/5 mL
INACTIVE INGREDIENTS: HYDROXYETHYL CELLULOSE, UNSPECIFIED; WATER; SACCHARIN SODIUM; DIMETHICONE; SORBIC ACID; SORBITOL SOLUTION; XANTHAN GUM; BENZYL ALCOHOL

FD antacid supreme cherry

Active ingredients (in each 5 mL teaspoonful)

Calcium carbonate 400 mg
Magnesium hydroxide 135 mg

Purpose

Antacid

Uses

relieves

- heartburn
- sour stomach
- acid indigestion
- upset stomach associated with these symptoms
- overindulgence in food and drink

Warnings

Ask a doctor before use if you have

- kidney disease
- a magnesium-restricted diet

Ask a doctor or pharmacist before use if you are presently taking a prescription drug.
Antacids may interact with certain prescription drugs.
Stop use and ask a doctor if symptoms last more than 2 weeks
If pregnant or breast-feeding, ask a health professional before use.

Keep out of reach of children.

Directions

- shake well before use
- adults and children 12 years and older: take 2 to 4 teaspoonfuls between meals, at bedtime, or as directed by a doctor
- do not take more than 18 teaspoonfuls in a 24 hour period or use the maximum dosage for more than 2 weeks
- children under 12 years: ask a doctor

Other information

- each 5 mL teaspoonful contains: calcium 160mg, magnesium 55 mg
- refrigerate after opening to preserve freshness and purity
- do not freeze
- keep tightly closed

Inactive ingredients

benzyl alcohol, flavor, hydroxyethylcellulose, purified water, saccharin sodium, simethicone emulsion, sorbic acid, sorbitol solution, xanthan gum

Questions or comments?

1-800-540-3765